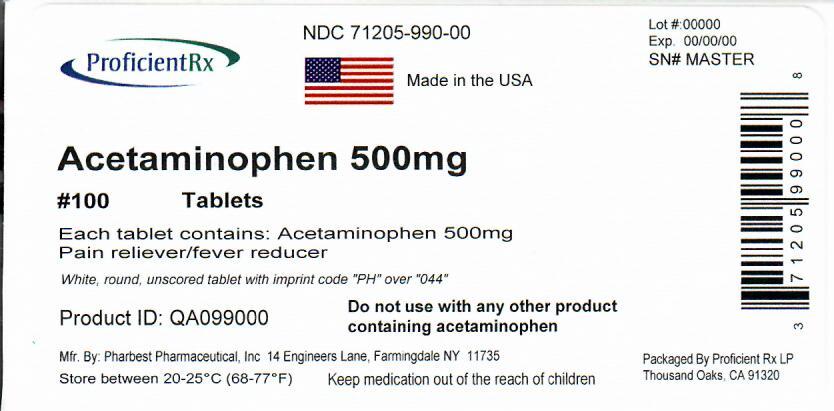 DRUG LABEL: Pharbetol
NDC: 71205-990 | Form: TABLET
Manufacturer: Proficient Rx LP
Category: otc | Type: HUMAN OTC DRUG LABEL
Date: 20240201

ACTIVE INGREDIENTS: ACETAMINOPHEN 500 mg/1 1
INACTIVE INGREDIENTS: POVIDONE K30; STARCH, CORN; SODIUM STARCH GLYCOLATE TYPE A POTATO; STEARIC ACID

Drug Facts

Active ingredient (in each tablet)

Acetaminophen 500mg

Purpose

Pain reliever/fever reducer

Uses

Temporarily relieves minor aches and pains due to:

- headache
- backache
- minor pain of arthritis
- toothache
- muscular aches
- menstrual cramps

Temporarily reduces fever

Warnings

Liver warning: This product contains acetaminophen. Severe liver damage may occur if you take

- more than 8 tablets in 24 hours, which is the maximum daily amount
- with other drugs containing acetaminophen
- 3 or more alcoholic drinks every day while using this product

Do not use

- With any other drug containing acetaminophen (prescription or nonprescription). If you are not sure whether a drug contains acetaminophen, ask a doctor or pharmacist
- if you are allergic to acetaminophen or any of the inactive ingredients in this product

Ask a doctor before use if you have

liver disease.

Ask a doctor or pharmacist before use if you are

taking the blood thinning drug warfarin

Stop use and ask a doctor if:

- Pain gets worse or lasts more than 10 days.
- Fever gets worse or lasts more than 3 days.
- New symptoms occur.
- Redness or swelling is present.

These could be signs of a serious condition.

If pregnant or breast-feeding,

ask a health professional before use.

Overdose warning:

Taking more than the recommended dose (overdose) may cause liver damage. In the case of overdose, get medical help or contact a Poison Control Center right away.

Directions

- do not take more than directed (see overdose warning).
- Adult and Children 12 years and over: take 2 tablets, every 4 to 6 hours while symptoms last. Do not take more than 8 tablets in 24 hours. Do not take for more than 10 days unless directed by a doctor.
- Children under 12 years: do not use adult extra strength product in children under 12 years of age; this will provide more than recommended dose (overdose) and may cause liver damage.

Inactive ingredients

Povidone, Pregelatinized corn starch, sodium starch glycolate, stearic acid.

Questions?

Adverse drug event call: (866) 562-2756

Repackaged by:

Proficient Rx LP

Thousand Oaks, CA 91320

PACKAGE LABEL

NDC 71205-990-00

Manufactured in the USA

Extra Strength *Compare to the active ingredient in Extra Strength Tylenol Caplet

Do not use any other product containing acetaminophen

Acetaminophen 500mg

Pain Reliever Fever Reducer

100 Tablets